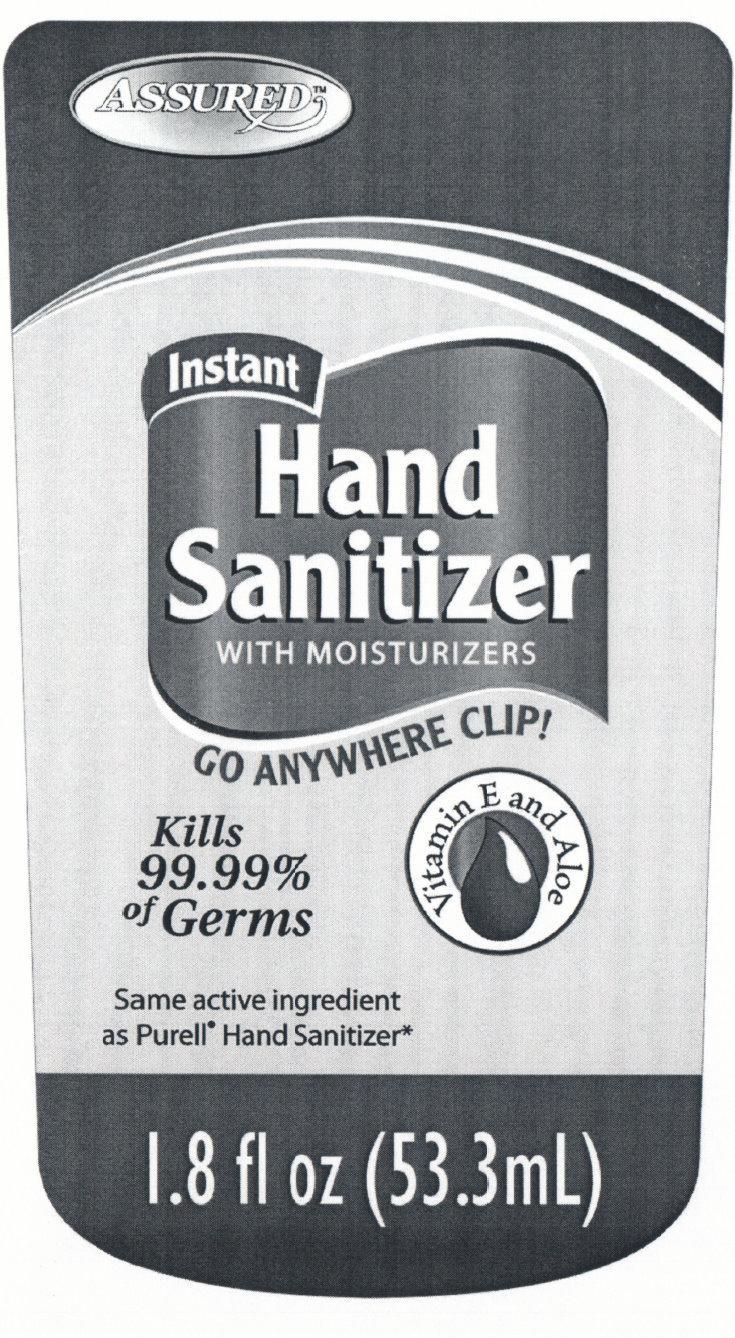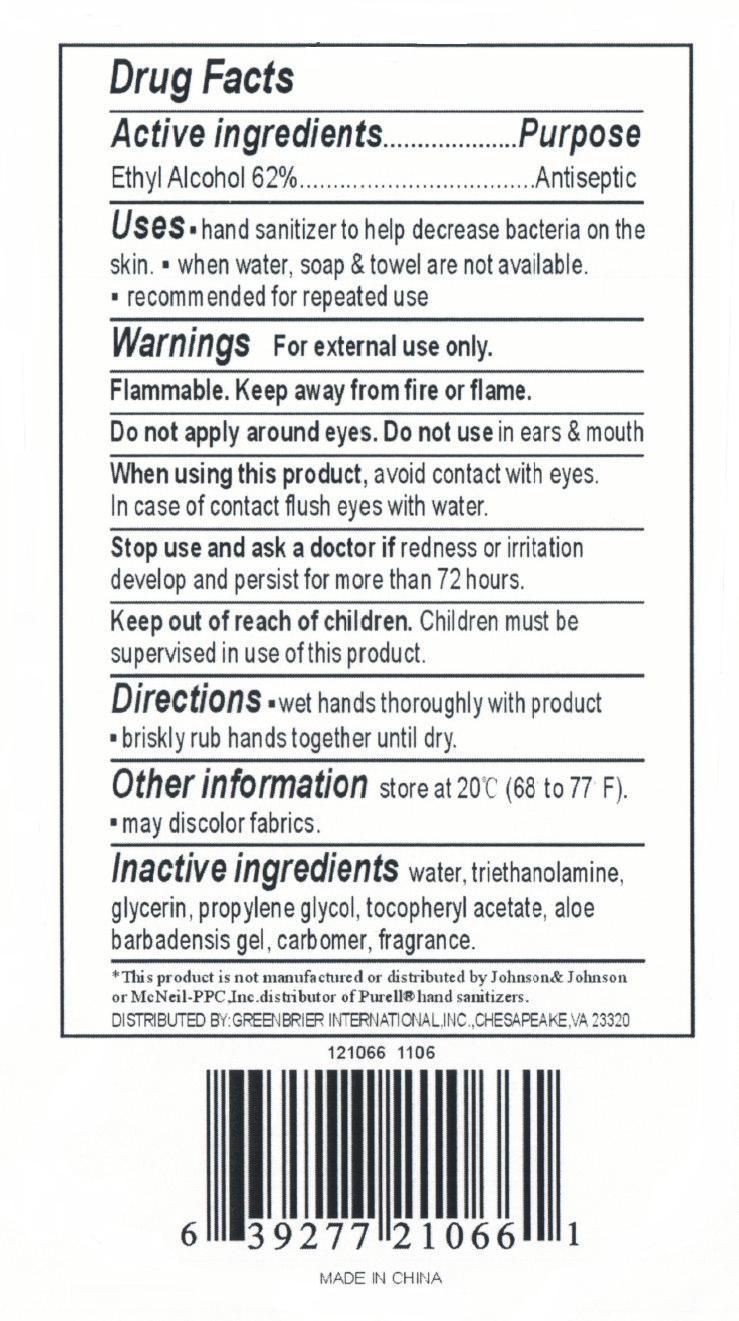 DRUG LABEL: ASSURED Instant Hand Sanitizer WITH MOISTURIZERS Vitamin E and Aloe 
NDC: 33992-1071 | Form: GEL
Manufacturer: Greenbrier International, Inc.
Category: otc | Type: HUMAN OTC DRUG LABEL
Date: 20150218

ACTIVE INGREDIENTS: ALCOHOL 62 mL/100 mL
INACTIVE INGREDIENTS: WATER; TROLAMINE; GLYCERIN; PROPYLENE GLYCOL; ALPHA-TOCOPHEROL ACETATE; ALOE VERA LEAF; CARBOMER HOMOPOLYMER TYPE C

ASSURED Instant Hand Sanitizer WITH MOISTURIZERS Vitamin E and Aloe

Drug Facts

Active Ingredients

Ethyl Alcohol 62%

Purpose
Antiseptic

Uses

- Hand sanitizer to help decrease bacteria on the skin.
- When water, soap and towel are not available.
- Recommended for repeated use.

Warnings For external use only.

SAFE HANDLING WARNING

Flammable. Keep away from fire or flame.

WHEN USING

Do not apply around eyes. Do not use in ears and mouth

When using this product, avoid contact with eyes.

In case of contact flush eyes with water.

Stop use and ask a doctor if redness or irritation develop and persist for more than 72 hours.

Keep out of reach of children. Children must be supervised in use of this product.

Directions

- wet hands thoroughly with product
- briskly rub hands together until dry.

Other Information

store at 20 degrees C (68 to 77 degrees F).

- may discolor fabrics.

Inactive Ingredients

water, triethanolamine , glycerin, propylene glycol, tocopheryl acetate, aloe barbadensis gel carbomer, fragrance.

DESCRIPTION

This product is not manufactured or distributed by Johnson and Johnson

or McNeil-PPC, Inc. distributor of Purell hand sanitizers.

Distributed By: GREENBRIAR INTERNATIONAL, INC.,

CHESAPEAKE, VA 23320

MADE IN CHINA

PACKAGE LABEL

ASSURED

Instant Hand Sanitizer

with Moisturizers

Vitamin E and Aloe

Kills 99.99 percent of Germs

Same active ingredient as Purell Hand Sanitizer

1.8 fl oz (53.3 ml)